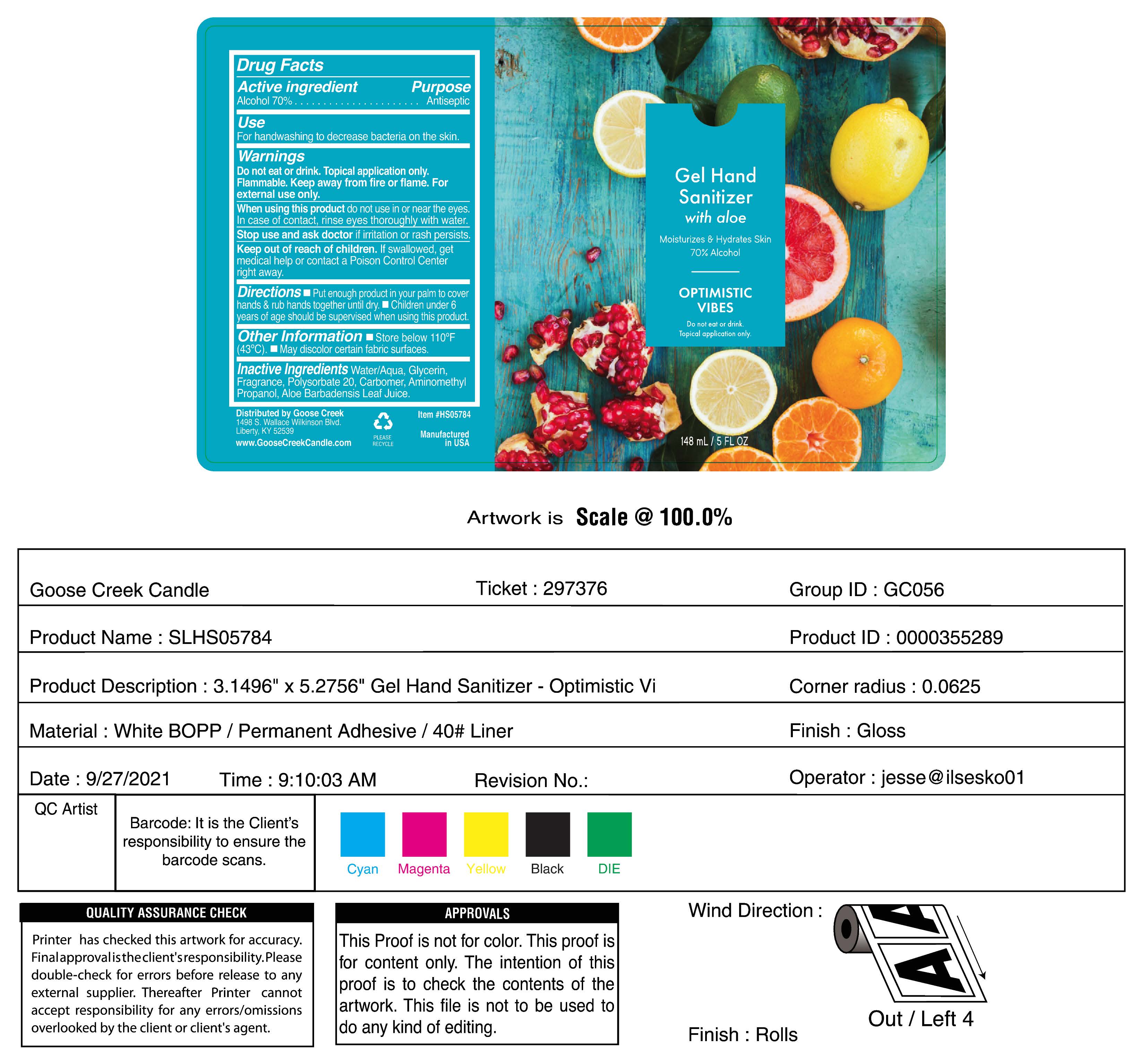 DRUG LABEL: Hand Sanitizer
NDC: 82463-076 | Form: LIQUID
Manufacturer: GOOSE CREEK CANDLES, LLC
Category: otc | Type: HUMAN OTC DRUG LABEL
Date: 20220816

ACTIVE INGREDIENTS: ALCOHOL 73.409 mL/100 mL
INACTIVE INGREDIENTS: GLYCERIN 1.495 mL/100 mL; WATER 22.52 mL/100 mL; CARBOMER HOMOPOLYMER, UNSPECIFIED TYPE 0.49 mL/100 mL; POLYSORBATE 20 0.98 mL/100 mL

Gel Hand Sanitizer with aloe Moisturizes & Hydrates Skin 70% Alcohol. Optimistic Vibes

Active Ingredient

Alcohol 70%

Purpose

Antiseptic

Use

For handwashing to decrease bacteria on the skin

Warnings

Do not eat or drink. Topical application only. Flammable. Keep away from fire or flame. For external use only.

When using this product do not use in or near the eyes. In case of contact, rinse eyes thoroughly with water.

Stop use and ask doctor if irritation or rash persists

Keep out of reach of children.

If swallowed, get medical help or contact a Poison Control Center right away

Directions

Put enough product in your palm to cover hands & rub together until dry. Children under 6 years of age should be supervised when using this product.

Other information

Store below 110 F (43C).

May discolor certain fabric surfaces

Inactive ingredient

Water/Aqua, Glycerin, Fragrance, Polysorbate 20, Carbomer, Aminomethyl Propanol, Aloe Barbadensis Leaf Juice